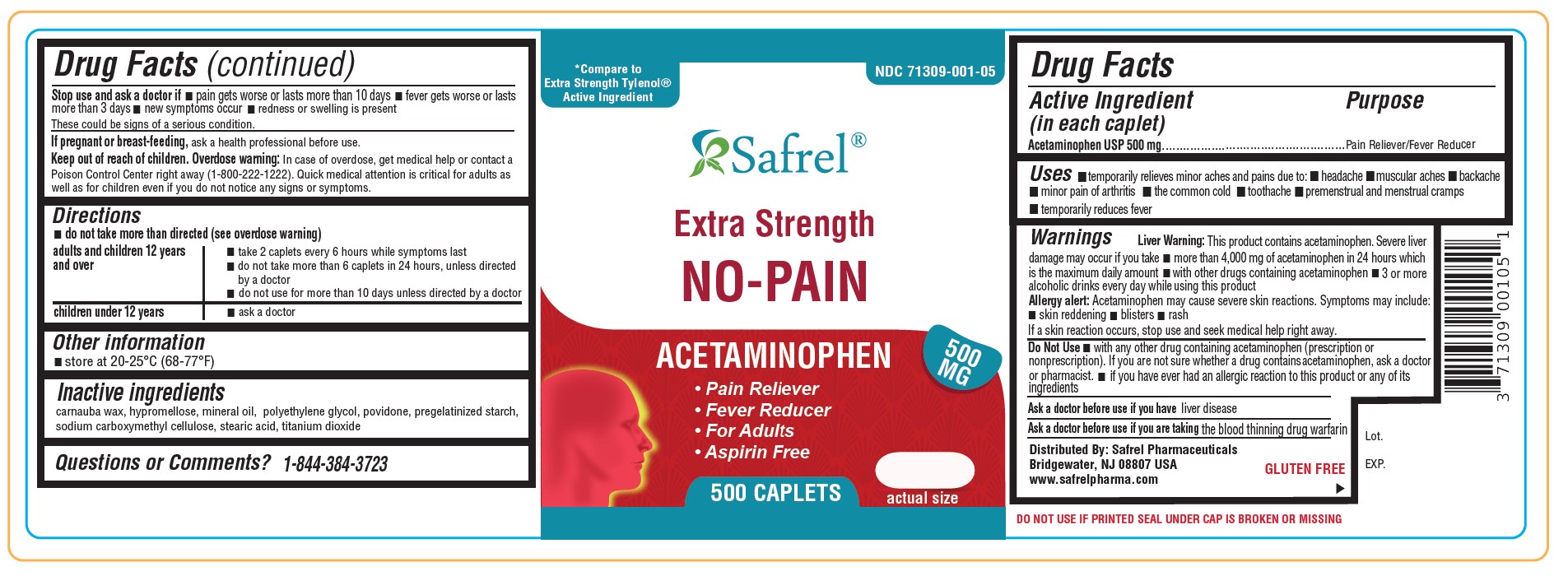 DRUG LABEL: Extra Strength No-Pain
NDC: 71309-001 | Form: TABLET
Manufacturer: Safrel Pharmaceuticals, LLC.
Category: otc | Type: HUMAN OTC DRUG LABEL
Date: 20250423

ACTIVE INGREDIENTS: ACETAMINOPHEN 500 mg/1 1
INACTIVE INGREDIENTS: STARCH, PREGELATINIZED CORN; POVIDONE; SILICON DIOXIDE; HYPROMELLOSES; CELLULOSE, MICROCRYSTALLINE; STEARIC ACID; POLYETHYLENE GLYCOL, UNSPECIFIED; TITANIUM DIOXIDE; TALC

Acetaminophen Extra Strength 500 mg

Active Ingredient

(in each tablet)

Acetaminophen 500mg

Purpose

Pain reliever/fever reducer

Uses

- temporary relieves minor aches and pains due to
- the common cold
- headache
- backache
- toothache
- muscular aches
- premenstrual and menstrual cramps and
- temporarily reduces fever

Warnings

Liver warning: This product contains acetaminophen. Severe liver damage may occur if you take

- more than 4,000 mg of acetaminophen in 24 hours
- with other drugs containing acetaminophen
- 3 or more alcoholic drinks every day while using this product

Allergy alert: Acetaminophen may cause severe skin reactions. Symptoms may include:

- skin reddening
- blisters
- rash

If a skin reaction occurs, stop use and seek medical help right away.

Do not use

- with any other drug containing acetaminophen (prescription or nonprescription). If you are not sure whether a drug contains acetaminophen, ask a doctor or pharmacist.
- if you have ever had an allergic reaction to this product or any of its ingredients

Ask a doctor before use if you have

- liver disease

Ask a doctor or pharmacist before use if you are

- taking the blood thinning drug warfarin

Stop use and ask a doctor if

- pain gets worse or lasts more than 10 days
- fever gets worse or lasts more than 3 days
- new symptoms occur
- redness or swelling is present

These could be signs of a serious condition.

If pregnant or breast-feeding

ask a health professional before use

Keep out of reach of children.

Overdose warning: Taking more than the reccomended dose (overdose) may cause liver damage. In case of overdose. get medical help or contact a Poison Control Center (1-800-222-1222) right away. Quick medical attention is critical for adults as well as for children even if you do not notice any signs or symptoms.
Do not exceed recommended dosage.

Directions

- do not use more than directed (see overdose warning)
- Adults and children 12 years of age and older:
- Take 2 caplets every 6 hours while symptoms last.
- Do not take more than 6 caplets in 24 hours, unless directed by a doctor
- Do not use more than 10 days unless directed by a doctor.
- Children under 12 years of age: Do not use this extra strength product. This will provide more than the recommended dose (overdose) and could cause serious health problems.

Other Information

- store at controlled room temperature 20-25°C (68-77°F).
- read all product information before using.
- TAMPER EVIDENT: DO NOT USE IF IMPRINTED SAFETY SEAL UNDER CAP IS BROKEN OR MISSING.

Inactive Ingredients

Hypromellose, Magnesium Stearate, Microcrystalline Cellulose, Pregelatinized Starch, Polyethylene Glycol, Polyvinyl Pyrolidone, Stearic Acid, Talc, Titanium Dioxide

Questions or Comments

1-844-384-3723 (Mon-Fri 9AM-5PM EST) or www.safrelpharma.com

PACKAGE LABEL.PRINCIPAL DISPLAY PANEL

* This product is not manufactured or distributed by McNeil-Consumer Healthcare, owner of the registered trademark Tylenol*.

NDC 71309-001-05 500 Caplets